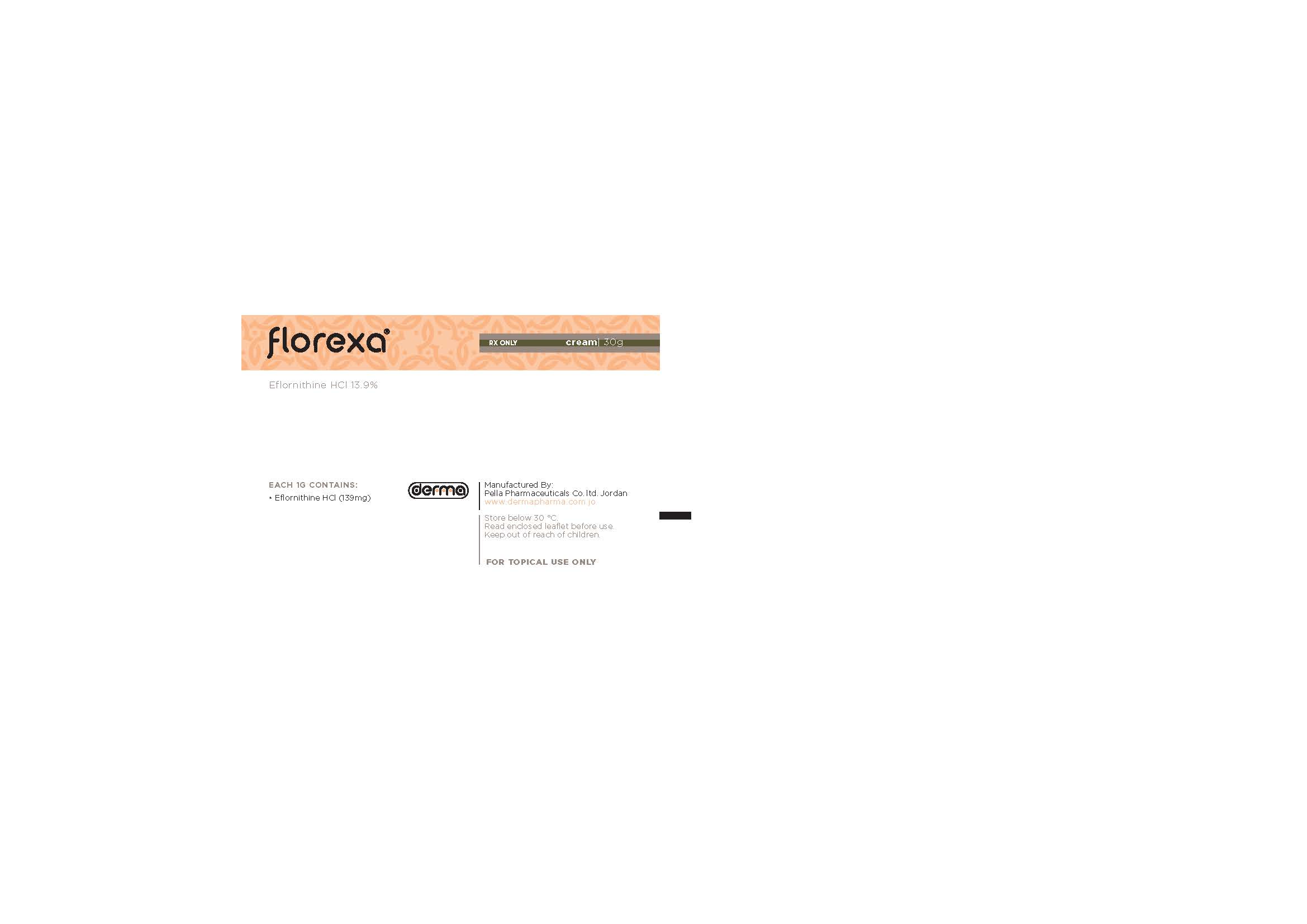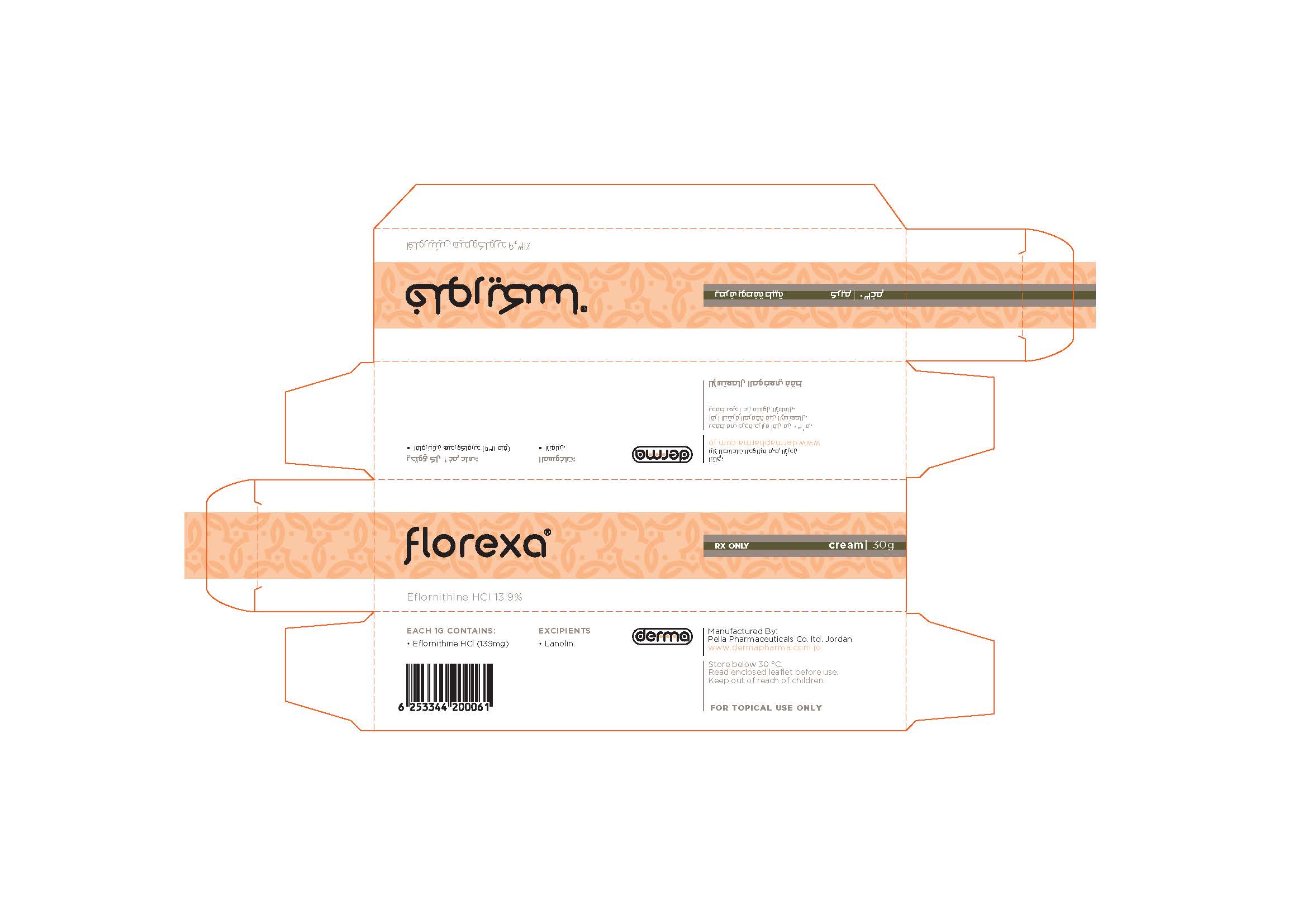 DRUG LABEL: Florexa
NDC: 82160-125 | Form: CREAM
Manufacturer: Pella Pharmaceuticals Co. Ltd
Category: prescription | Type: HUMAN PRESCRIPTION DRUG LABEL
Date: 20241231

ACTIVE INGREDIENTS: EFLORNITHINE HYDROCHLORIDE 4170 mg/30 g

Florexa

Composition

Each 1 g contains: Eflornithine hydrochloride 139 mg.
Excipients: Ceteareth-25, Cetostearyl alcohol, Lanolin, Glyceryl monostearate, mineral oil, Cetyl alcohol, Methyl Paraben, Emulsifying wax, Dimethicone, and Purified Water.

Properties

Florexa is a prescribed medication applied to the skin for the reduction of unwanted facial hair in women.
There are no studies examining the inhibition of the enzyme ornithine decarboxylase (ODC) in human skin following the application of topical eflornithine. However, there are studies in the literature that report the inhibition of ODC activity in skin following oral eflornithine. It is postulated that topical eflornithine hydrochloride irreversibly inhibits skin ODC activity. This enzyme is necessary in the synthesis of polyamines. Animal data indicate that inhibition of ornithine decarboxylase inhibits cell division and synthetic functions, which affect the rate of hair growth. Eflornithine hydrochloride Cream 13.9% has been shown to retard the rate of hair growth in non-clinical and clinical studies.

Indications

Florexa is indicated for the reduction of unwanted facial hair in women. Florexa has only been studied on the face and adjacent involved areas under the chin of affected individuals. Usage should be limited to these areas of involvement.

Contraindications

Eflomithine HCl is contraindicated in patients with a history of sensitivity to any components of the preparation.
Children less than 12 years of age shouldn't use Florexa.

Precautions

For external use only.
Transient stinging or burning may occur when applied to abraded or broken skin.

Pregnancy

Because there are no adequate and well-controlled studies in pregnant women, the risk / benefit ratio of using eflornithine HCl in women with unwanted facial hair who are pregnant should be weighed carefully with serious consideration for either not implementing or discontinuing use of Florexa.

Lactation

It is not known whether or not eflornithine hydrochloride is excreted in human milk. Caution should be exercised when Florexa is administered to a nursing woman.

Drug Interactions

It is not known if Eflornithine HCl has any interaction with other topically applied drug products.

Warnings

Discontinue use if hypersensitivity occurs.

Dosage and Administration

Apply a thin layer of Florexa, to wanted areas of the face and adjacent involved areas under the chin and rub in thoroughly. Do not wash treated area for at least 4 hours. Use twice daily at least 8 hours apart or as directed by a physician. The patient should continue to use hair removal techniques as needed in conjunction with Florexa. (Florexa should be applied at least 5 minutes after hair removal.) Cosmetics or sunscreens may be applied over treated areas; you should wait a few minutes to allow the treatment to be absorbed.

Florexa doesn't permanently remove hair or "cure" unwanted facial hair. It is not a depilatory. Your treatment program should include continuation of any hair removal technique you are currently using. Florexa will help you manage your condition and improve your appearance.

Improvement in the condition occurs gradually. Don't be discouraged if you see no immediate improvement. Be patient. Improvement may be seen as early as 4 to 8 weeks of treatment. Improvement may take longer in some individuals. If no improvement is seen after 6 months of use; discontinue use.

Overdosage

Overdosage information is unavailable.

Side Effects

The following side effects have been reported
Acne, Pseudofolliculitis Barbae, Stinging Skin, Headache, Burning Skin, Dry Skin, Pruritus (itching), Erythema (redness), Tingling Skin, Dyspepsia, skin irritation, rash, alopecia, dizziness, folliculitis, hair ingrown, facial edema, anorexia, nausea, asthenia, vertigo.

Storage

Store below 30 ºC.

How supplied

30 g packs

THIS IS A MEDICAMENT

- Medicament is a product which affects your health and its consumption contrary to instructions is dangerous for you.
- Strictly follow the doctor's prescription, the method of use and the instruction of the pharmacist who sold the medicament.
- The doctor and the pharmacist are experts in medicine, its benefits and risks.
- Do not by yourself interrupt the period of treatment prescribed for you.

Do not repeat the same prescription without consulting your doctor.

- Keep medicament out of reach of children.